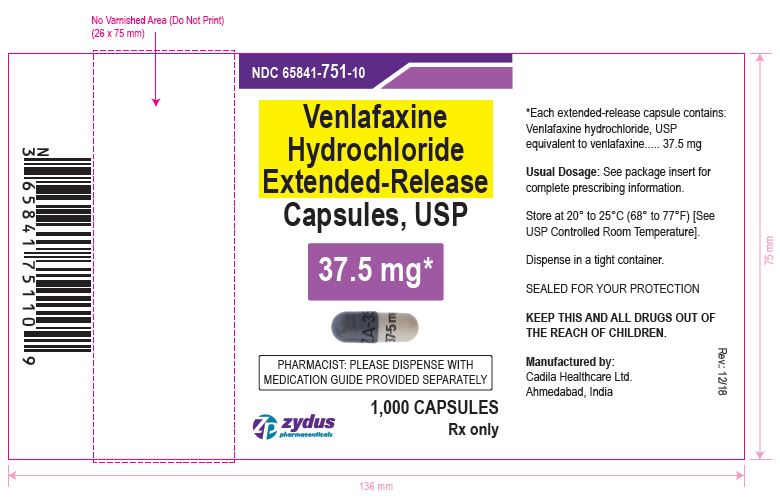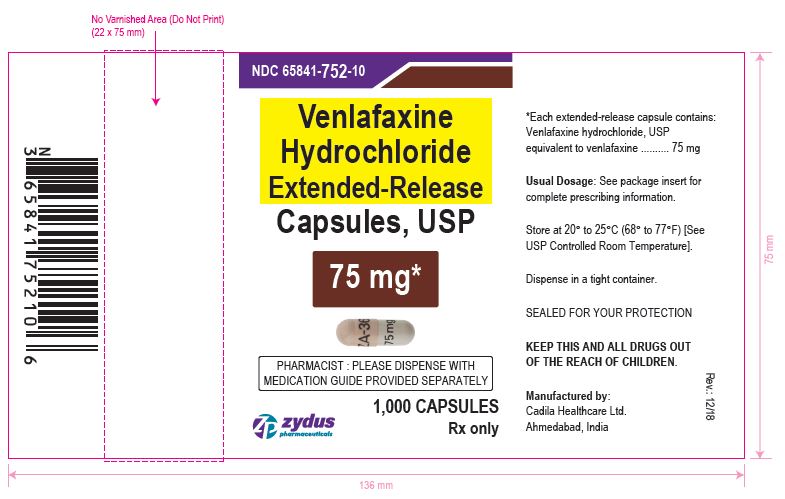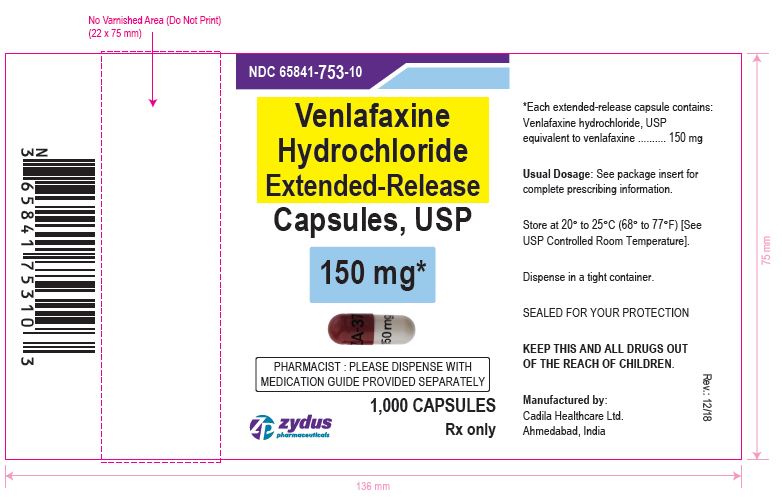 DRUG LABEL: venlafaxine hydrochloride
NDC: 65841-751 | Form: CAPSULE, EXTENDED RELEASE
Manufacturer: Zydus Lifesciences Limited
Category: prescription | Type: HUMAN PRESCRIPTION DRUG LABEL
Date: 20230928

ACTIVE INGREDIENTS: VENLAFAXINE HYDROCHLORIDE 37.5 mg/1 1
INACTIVE INGREDIENTS: FERROSOFERRIC OXIDE; HYPROMELLOSES; GELATIN; SODIUM LAURYL SULFATE; TALC; TITANIUM DIOXIDE; CETOSTEARYL ALCOHOL; SILICON DIOXIDE; CELLULOSE, MICROCRYSTALLINE; ETHYL ACRYLATE AND METHYL METHACRYLATE COPOLYMER (2:1; 750000 MW)

VENLAFAXINE HYDROCHLORIDE EXTENDED-RELEASE CAPSULES

PACKAGE LABEL.PRINCIPAL DISPLAY PANEL

NDC 65841-751-10

Venlafaxine Hydrochloride Extended-release Capsules USP, 37.5 mg

1000 Capsules

Rx only

NDC 65841-752-10

Venlafaxine Hydrochloride Extended-release Capsules USP, 75 mg

1000 Capsules

Rx only

NDC 65841-753-10

Venlafaxine Hydrochloride Extended-release Capsules USP, 150 mg

1000 Capsules

Rx only